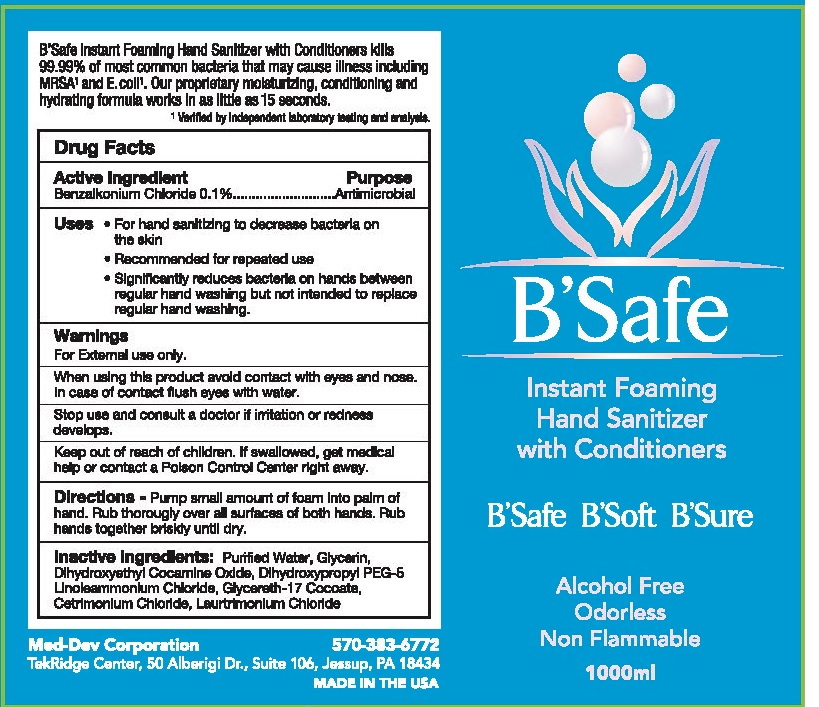 DRUG LABEL: BSafe Instant Foaming Hand Sanitizer
NDC: 69348-100 | Form: AEROSOL, FOAM
Manufacturer: Med-Dev Corporation
Category: otc | Type: HUMAN OTC DRUG LABEL
Date: 20141219

ACTIVE INGREDIENTS: BENZALKONIUM CHLORIDE 1 mg/1000 mL
INACTIVE INGREDIENTS: WATER; GLYCERIN; DIHYDROXYETHYL COCAMINE OXIDE; DIHYDROXYPROPYL PEG-5 LINOLEAMMONIUM CHLORIDE; GLYCERETH-17 COCOATE; CETRIMONIUM CHLORIDE; LAURTRIMONIUM CHLORIDE

B’Safe Instant Foaming Hand Sanitizer with Conditioners

Active ingredient

Benzalkonium Chloride 0.1%

Purpose

Antimicrobial

Uses

- For hand sanitizing to decrease bacteria on the skin
- Recommended for repeated use
- Significantly reduces bacteria on hands between regular hand washing but not intended to replace regular hand washing.

Warnings

For External use only.

When using this product avoid contact with eyes and nose. In case of contact flush eyes with water.

Stop use and consult a doctor if irritation or redness develops.

Keep out of reach of children.

If swallowed, get medical help or contact a Poison Control Center right away.

Directions

Pump small amount of foam into palm of hand. Rub thoroughly over all surfaces of both hands. Rub hands together briskly until dry.

Inactive ingredients

Purified Water, Glycerin, Dihydroxyethyl Cocamine Oxide, Dihydroxypropyl PEG-5 Linoleammonium Chloride, Glycereth-17 Cocoate, Cetrimonium Chloride, Laurtrimonium Chloride

Package/Label Principal Display Panel - Carton Label

B’Safe
Instant Foaming
Hand Sanitizer
with Conditioners

B’Safe B’Soft B’Sure

Alcohol Free
Odorless
Non Flammable

1000ml

Med-Dev Corporation
TekRidge Center, 50 Alberigi Dr., Suite 106, Jessup, PA 18434

570-383-6772

MADE IN THE USA

Carton Label